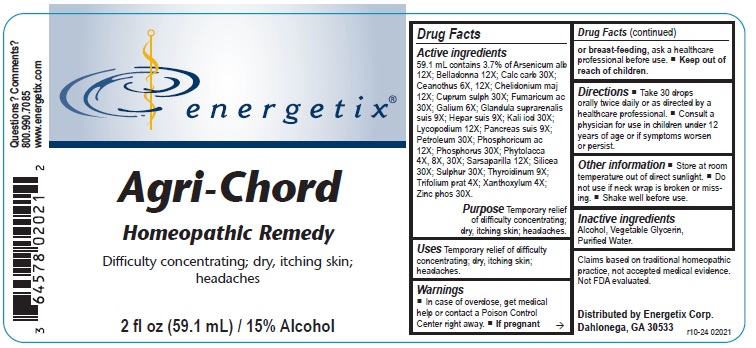 DRUG LABEL: Agri-Chord
NDC: 64578-0156 | Form: LIQUID
Manufacturer: Energetix Corporation
Category: homeopathic | Type: HUMAN OTC DRUG LABEL
Date: 20250711

ACTIVE INGREDIENTS: ARSENIC TRIOXIDE 12 [hp_X]/59.1 mL; ATROPA BELLADONNA 12 [hp_X]/59.1 mL; OYSTER SHELL CALCIUM CARBONATE, CRUDE 30 [hp_X]/59.1 mL; CEANOTHUS AMERICANUS LEAF 6 [hp_X]/59.1 mL; CHELIDONIUM MAJUS 12 [hp_X]/59.1 mL; CUPRIC SULFATE 30 [hp_X]/59.1 mL; FUMARIC ACID 30 [hp_X]/59.1 mL; GALIUM APARINE 6 [hp_X]/59.1 mL; SUS SCROFA ADRENAL GLAND 9 [hp_X]/59.1 mL; PORK LIVER 9 [hp_X]/59.1 mL; POTASSIUM IODIDE 30 [hp_X]/59.1 mL; LYCOPODIUM CLAVATUM SPORE 12 [hp_X]/59.1 mL; SUS SCROFA PANCREAS 9 [hp_X]/59.1 mL; KEROSENE 30 [hp_X]/59.1 mL; PHOSPHORIC ACID 12 [hp_X]/59.1 mL; PHOSPHORUS 30 [hp_X]/59.1 mL; PHYTOLACCA AMERICANA ROOT 4 [hp_X]/59.1 mL; SARSAPARILLA 12 [hp_X]/59.1 mL; SILICON DIOXIDE 30 [hp_X]/59.1 mL; SULFUR 30 [hp_X]/59.1 mL; THYROID, UNSPECIFIED 9 [hp_X]/59.1 mL; TRIFOLIUM PRATENSE FLOWER 4 [hp_X]/59.1 mL; ZANTHOXYLUM AMERICANUM BARK 4 [hp_X]/59.1 mL; ZINC PHOSPHIDE 30 [hp_X]/59.1 mL
INACTIVE INGREDIENTS: ALCOHOL; GLYCERIN; WATER

Agri-Chord

Active ingredients

59.1 mL contains 3.7% of Aresenicum alb 12X; Belladonna 12X; Calc carb 30X; Ceanothus 6X, 12X; Chelidonium maj 12X; Cuprum sulph 30X; Fumaricum ac 30X; Galium 6X; Glandula suprarenalis suis 9X; Hepar suis 9X; Kali iod 30X; Lycopodium 12X; Pancreas suis 9X; Petroleum 30X; Phosphoricum ac 12X; Phosphorus 30X; Phytolacca 4X, 8X, 30X; Sarsaparilla 12X; Silicea 30X; Sulphur 30X; Thyroidinum 9X; Trifolium prat 4X; Xanthoxylum 4X; Zinc phos 30X.

Claims based on traditional homeopathic practice, not accepted medical evidence. Not FDA evaluated.

Uses

Temporary relief of difficulty concentrating; dry, itching skin; headaches.

Warnings

- In case of overdose, get medical help or contact a Poison Control Center right away.
- If pregnant or breast-feeding, ask a healthcare professional before use.

• Keep out of reach of children.

Directions

• Take 30 drops orally twice daily or as directed by a healthcare professional.

• Consult a physician for use in children under 12 years of age or if symptoms worsen of persist.

Other information

• Store at room temperature out of direct sunlight.

• Do not use if neck wrap is broken or missing,

• Shake well before use.

Inactive ingredients

Alcohol, Vegetable Glycerin, Purified Water.

QUESTIONS

Distributed by Energetix Corp.

Dahlonega, GA 30533

Questions? Comments?

800.990.7085

www.energetix.com

PACKAGE LABEL

energetix

Agri-Chord

Homeopathic Remedy

Difficulty concentrating; dry, itching skin;

headaches

2 fl oz (59.1 mL) / 15% Alcohol

PURPOSE

Purpose Temporary relief of difficulty concentrating; dry, itching skin; headaches.